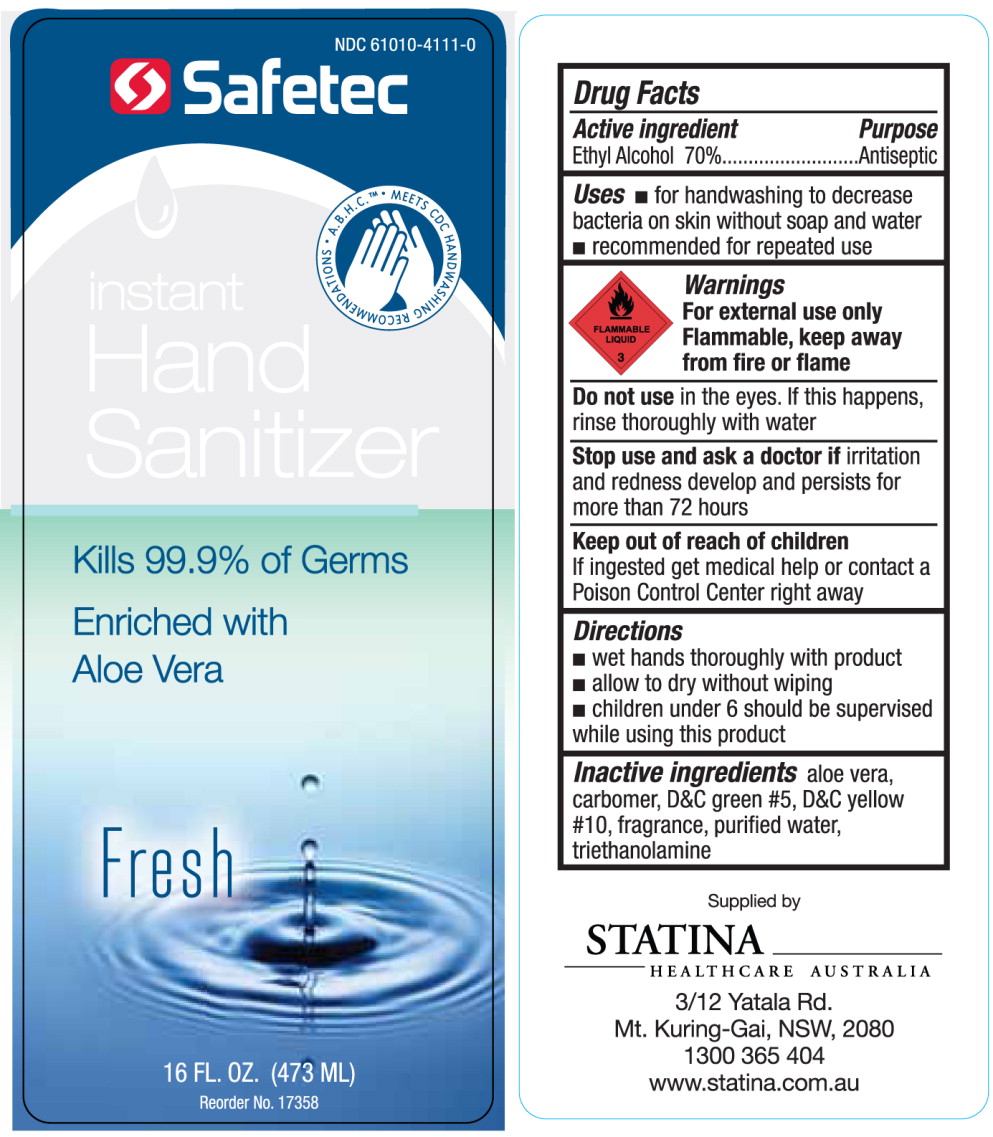 DRUG LABEL: Instant Hand Sanitizer
NDC: 61010-4111 | Form: GEL
Manufacturer: Safetec of America
Category: otc | Type: HUMAN OTC DRUG LABEL
Date: 20100915

ACTIVE INGREDIENTS: alcohol 0.7 g/1 mL
INACTIVE INGREDIENTS: aloe; water; trolamine

INSTANT HAND SANITIZER – alcohol gel

Safetec of America, Inc.

Instant Hand Sanitizer

Drug Facts

Active Ingredient

Ethyl Alcohol 70%

Purpose

Antiseptic

Uses

- for handwashing to decrease bacteria on skin without soap and water
- recommended for repeated use

Warnings

For external use only

Flammable, keep away from fire or flame

Do not use in the eyes. If this happens, rinse thoroughly with water

Stop use and ask a doctor if irritation and redness develop and persists for more than 72 hours

Keep out of reach of children

If ingested get medical help or contact a Poison Control Center right away

Directions

- wet hands thoroughly with product
- allow to dry without wiping
- children under 6 should be supervised while using this product

Inactive ingredients

aloe vera, carbomer, D&C green #5, D&C yellow#10, fragrance, purified water, triethanolamine

Supplied by

STATINA

HEALTHCARE AUSTRALIA

3/12 Yatala Rd.

Mt. Kuring-Gai, NSW, 2080

1300 365 404

www.statina.com.au

PRINCIPAL DISPLAY PANEL

NDC 61010-4111-0

Safetec

instant

Hand

Sanitizer

Kills 99.9% of Germs

Enriched with

Aloe Vera

Fresh

16 FL. OZ. (473 ML)

Reorder No. 17358